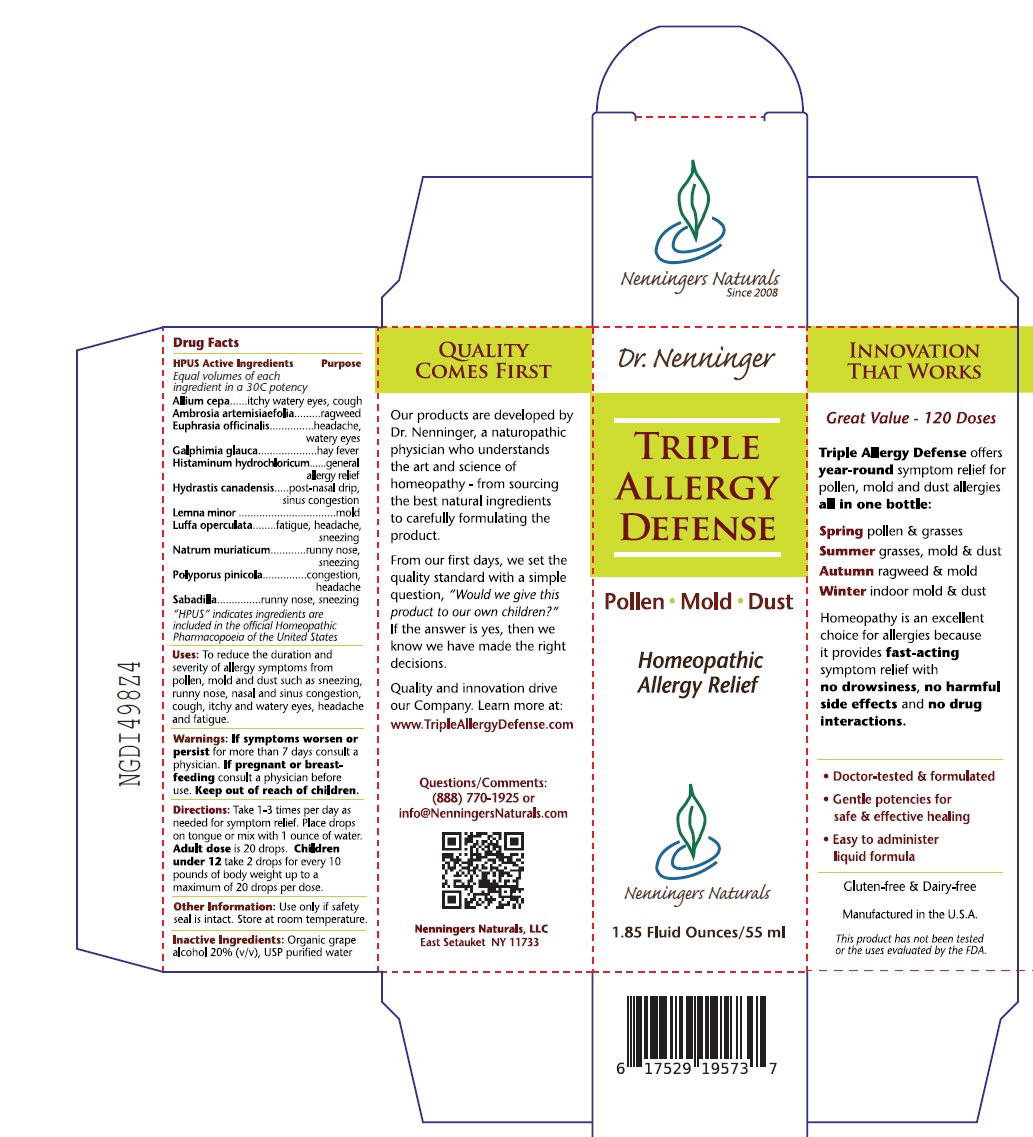 DRUG LABEL: Triple Allergy Defense
NDC: 42731-033 | Form: LIQUID
Manufacturer: Nenningers Naturals, LLC
Category: homeopathic | Type: HUMAN OTC DRUG LABEL
Date: 20251225

ACTIVE INGREDIENTS: GALPHIMIA GLAUCA FLOWERING TOP 30 [hp_C]/60 mL; HISTAMINE DIHYDROCHLORIDE 30 [hp_C]/60 mL; HYDRASTIS CANADENSIS WHOLE 30 [hp_C]/60 mL; LEMNA MINOR 30 [hp_C]/60 mL; LUFFA OPERCULATA FRUIT 30 [hp_C]/60 mL; SODIUM CHLORIDE 30 [hp_C]/60 mL; ALLIUM CEPA WHOLE 30 [hp_C]/60 mL; AMBROSIA ARTEMISIIFOLIA 30 [hp_C]/60 mL; EUPHRASIA STRICTA 30 [hp_C]/60 mL; FOMITOPSIS PINICOLA FRUITING BODY 30 [hp_C]/60 mL; SCHOENOCAULON OFFICINALE SEED 30 [hp_C]/60 mL
INACTIVE INGREDIENTS: ALCOHOL; WATER

Dr. Nenninger Triple Allergy Defense

Drug Facts

Uses: To reduce the duration and severity of allergy symptoms from pollen, mold and dust such as sneezing, runny nose, nasal and sinus congestion, cough, itchy and watery eyes, headache and fatigue.

PURPOSE

Homeopathic Allergy Relief

DOSAGE AND ADMINISTRATION

Directions: Take 1 to 3 times per day as needed for symptom relief. Place drops on the tongue or mix with 1 ounce of water. Adult dose is 20 drops. Children under 12 take 2 drops for every 10 pounds of body weight up to a maximum of 20 drops per dose.

HPUS Active Ingredients

Allium cepa, Ambrosia artemisiaefolia, Euphrasia officinalis, Galphimia glauca, Histaminum hydrochloricum, Hydrastis canadensis, Lemna minor, Luffa operculata, Natrum muriaticum, Polyporus pinicola, Sabadilla

Equal volumes of each ingredient in a 30C potency.

* HPUS indicates ingredients are monographed in the official Homeopathic Pharmacopeia of the United States” to “HPUS indicates ingredients are included in the official Homeopathic Pharmacopoeia of the United States.

Inactive Ingredients: Organic grape alcohol USP water

Warnings

ASK DOCTOR

If symptoms worsen or persist for more than 7 days consult a physician.

PREGNANCY OR BREAST FEEDING

If pregnant or breastfeeding consult a physician before use.

Keep out of reach of children.

OTHER SAFETY INFORMATION

Use only if the safety seal is intact. Store at room temperature, away from direct sunlight.

PACKAGE LABEL

Dr. Nenninger

Triple Allergy Defense

Pollen * Mold * Dust

Homeopathic Allergy Relief

1.85 Fluid Ounces/55 ml